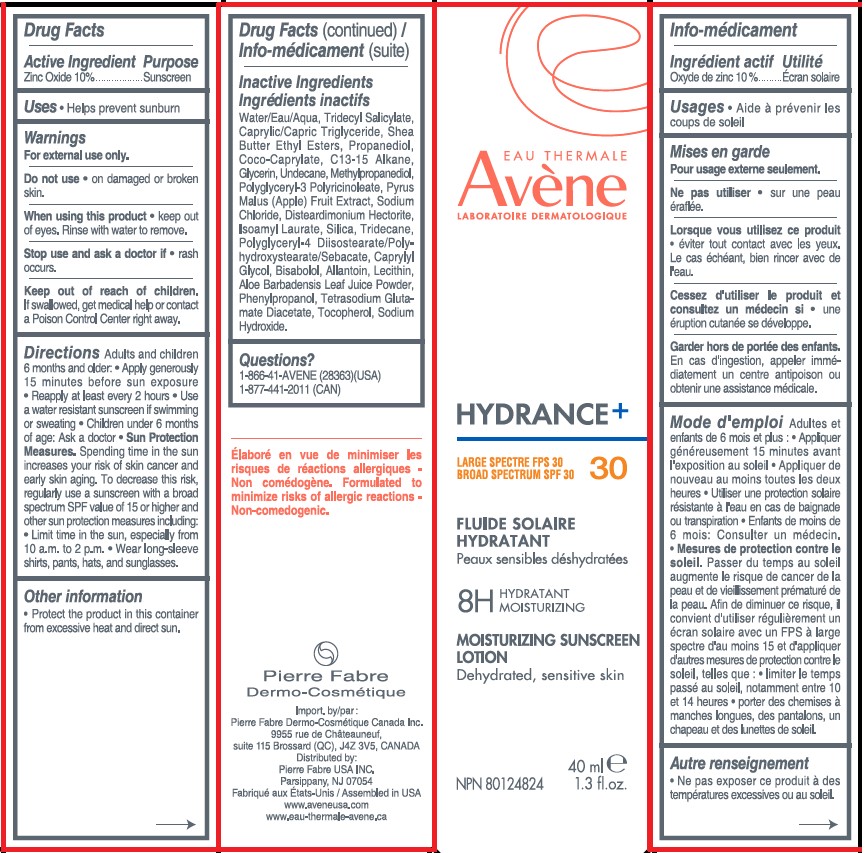 DRUG LABEL: Avene Hydrance Moisturizing SPF 30
NDC: 64760-783 | Form: LOTION
Manufacturer: Pierre Fabre USA Inc.
Category: otc | Type: HUMAN OTC DRUG LABEL
Date: 20240311

ACTIVE INGREDIENTS: ZINC OXIDE 100 mg/1 mL
INACTIVE INGREDIENTS: TRIDECYL SALICYLATE; COCO-CAPRYLATE; C13-15 ALKANE; DISTEARDIMONIUM HECTORITE; SILICON DIOXIDE; CAPRYLYL GLYCOL; SODIUM CHLORIDE; WATER; TOCOPHEROL; METHYLPROPANEDIOL; SHEA BUTTER ETHYL ESTERS; PROPANEDIOL; POLYGLYCERYL-4 DIISOSTEARATE/POLYHYDROXYSTEARATE/SEBACATE; GLYCERIN; POLYGLYCERYL-3 PENTARICINOLEATE; APPLE; ALLANTOIN; PHENYLPROPANOL; TETRASODIUM GLUTAMATE DIACETATE; SODIUM HYDROXIDE; TRIDECANE; MEDIUM-CHAIN TRIGLYCERIDES; UNDECANE; ISOAMYL LAURATE; LEVOMENOL; LECITHIN, SOYBEAN; ALOE VERA LEAF

Avene Hydrance Moisturizing Sunscreen Lotion SPF 30

Active ingredient

Zinc oxide 10%

Purpose

Sunscreen

Uses

• helps prevent sunburn.

Warnings

For external use only.

Do not use

• on broken skin.

When using this product

• keep out of eyes. Rinse with water to remove.

Stop use and ask a doctor if

• rash occurs.

Keep out of reach of children.

If swallowed, call a poison control center or get medical help right away.

Directions

Adults and children 6 months and older:

• Apply generously 15 minutes before sun exposure • Reapply: • at least every 2 hours • Use a water resistant sunscreen if swimming or sweating • Children under 6 months of age: Ask a doctor • Sun Protection Measures. Spending time in the sun increases your risk of skin cancer and early skin aging. To decrease this risk, regularly use a sunscreen with a broad spectrum SPF value of 15 or higher and other sun protection measures including: • Limit time in the sun, especially from 10 a.m. to 2 p.m. • Wear long-sleeve shirts, pants, hats, and sunglasses.

Inactive Ingredients

Water, Tridecyl Salicylate, Caprylic/Capric Triglyceride, Shea Butter Ethyl Esters, Propanediol, Coco-Caprylate, C13-15 Alkane, Glycerin, Undecane, Methylpropanediol, Polyglyceryl-3 Polyricinoleate, Pyrus Malus (Apple) Fruit Extract, Sodium Chloride, Disteardimonium Hectorite, Isoamyl Laurate, Silica, Tridecane, Polyglyceryl-4 Diisostearate/Polyhydroxystearate/Sebacate, Caprylyl Glycol, Bisabolol, Allantoin, Lecithin, Aloe Barbadensis Leaf Juice Powder, Phenylpropanol, Tetrasodium Glutamate Diacetate, Tocopherol, Sodium Hydroxide.

Other Information

• Protect this product in this container from excessive heat and direct sun.

Questions?

1-866-41-AVENE (28363)

1-877-441-2011 (CAN)